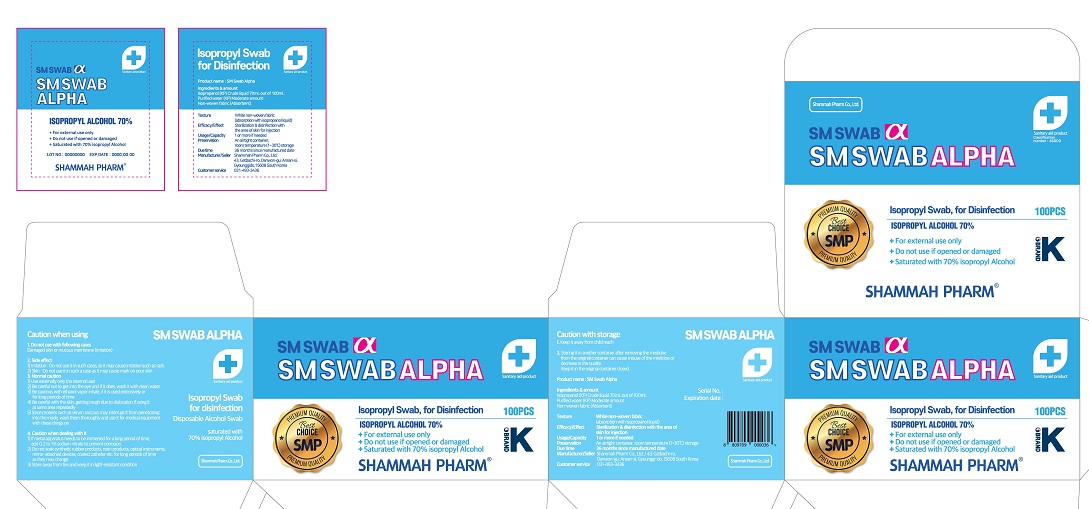 DRUG LABEL: SM SWABALPHA
NDC: 75697-0007 | Form: LIQUID
Manufacturer: shammah pharm
Category: otc | Type: HUMAN OTC DRUG LABEL
Date: 20210117

ACTIVE INGREDIENTS: ISOPROPYL ALCOHOL 70 mL/100 mL
INACTIVE INGREDIENTS: WATER

Drug Facts

ACTIVE INGREDIENT

isopropyl alcohol

PURPOSE

sterilization of hands, skin and so on

KEEP OUT OF REACH OF THE CHILDREN

INDICATIONS AND USAGE

take appropriate amount on the hand, rub and dry well

WARNINGS

■ Flammable. Keep away from fire or flame.

■ For external use only.

■ Do not use in eyes.

■ lf swallowed, get medical help promptly.

■ Stop use, ask doctor lf irritation occurs.

■ Keep out of reach of children.

DOSAGE AND ADMINISTRATION

for external use only

INACTIVE INGREDIENT

purified water, non-woven fabric